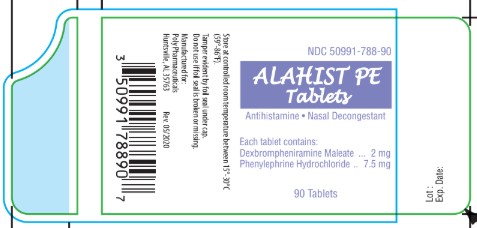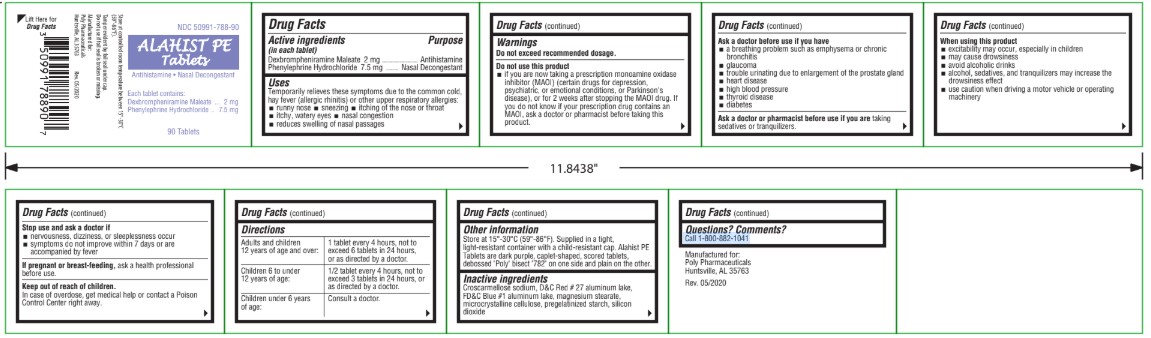 DRUG LABEL: Alahist PE
NDC: 50991-788 | Form: TABLET
Manufacturer: Poly Pharmaceuticals, Inc.
Category: otc | Type: HUMAN OTC DRUG LABEL
Date: 20251203

ACTIVE INGREDIENTS: DEXBROMPHENIRAMINE MALEATE 2 mg/1 1; PHENYLEPHRINE HYDROCHLORIDE 7.5 mg/1 1
INACTIVE INGREDIENTS: MAGNESIUM STEARATE; FD&C BLUE NO. 1; SILICON DIOXIDE; CROSCARMELLOSE SODIUM; STARCH, CORN; D&C RED NO. 27; MICROCRYSTALLINE CELLULOSE

Alahist PE

Active Ingredients

(in each tablet)
Dexbrompheniramine Maleate 2 mg
Phenylephrine Hydrochloride 7.5 mg

Purpose

Dexbrompheniramine Maleate- -Antihistamine
Phenylephrine Hydrochloride-- Nasal Decongestant

Uses

Temporarily relieves these symptoms due to the common cold, hay fever (allergic rhinitis) or other upper respiratory allergies:

- runny nose
- sneezing
- itching of the nose or throat
- itchy, water eyes
- nasal congestion
- reduces swelling of nasal passages

Warnings

Do not use this product

if you are now taking a prescription monoamine oxidase inhibitor (MAOI) (certain drugs for depression, psychiatric, or emotional conditions, or Parkinson's disease), or for 2 weeks after stopping the MAOI drug. If you do not know if your prescription drug contains an MAOI, ask a doctor or pharmacist before taking this product.

Ask a doctor before use if you have

- a breathing problem such as emphysema or chronic bronchitis
- glaucoma
- trouble urinating due to enlargement of the prostate gland
- heart disease
- high blood pressure
- thyroid disease
- diabetes

Ask a doctor or pharmacist before use if you are taking
sedatives or tranquilizers.

When Using This product

- excitability may occur, especially in children
- may cause drowsiness
- avoid alcoholic drinks
- alcohol, sedatives, and tranquilizers may increase the drowsiness effect
- use caution when driving a motor vehicle or operating machinery

Stop use and Ask Doctor if

- nervousness, dizziness, or sleeplessness occur
- symptoms do not improve within 7 days or are accompanied by fever

If Pregnant or Breastfeeding

ask a health professional before use.

Keep out of reach of children

In case of overdose, get medical help or contact a Poison Control Center right away.

Directions

Adults and children 12 years of age and over: | 1 tablet every 4 hours, not to exceed 6 tablets in 24 hours, or as directed by a doctor.
Children 6 to under 12 years of age | 1/2 tablet every 4 hours, not to exceed 3 tablets in 24 hours, or as directed by a doctor.
Children under 6 years of age: | Consult a doctor.

Other Information

Store at 15°-30°C (59°-86°F). Supplied in a tight,light-resistant container with a child-resistant cap. Alahist PE Tablets are dark purple, caplet-shaped, scored tablets, debossed "Poly" bisect "782" on one side and plain on the other.

Inactive ingredients

Croscarmellose sodium, D&C Red # 27 aluminum lake, FD&C Blue #1 aluminum lake, magnesium stearate, microcrystalline cellulose, pregelatinized starch, silicon dioxide

Questions? Comments?

Call 1-800-882-1041

Alahist PE Label

Manufactured for

Poly Pharmaceuticals
Huntsville, AL 35763